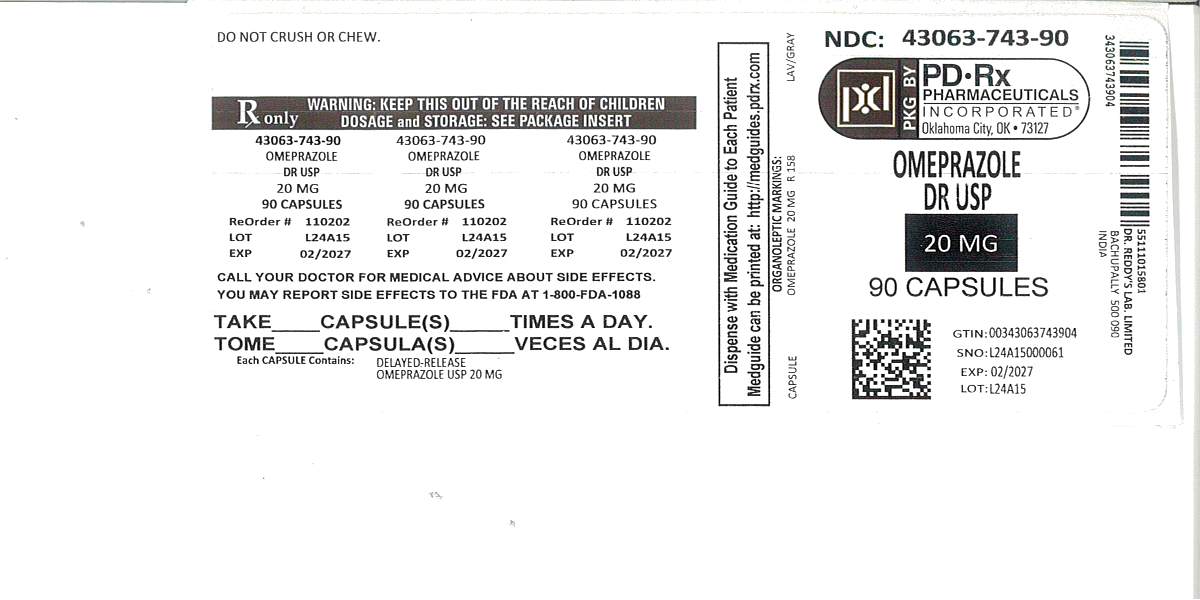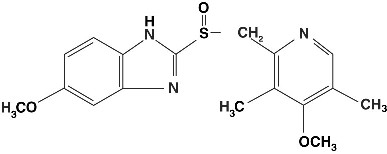 DRUG LABEL: Omeprazole
NDC: 43063-743 | Form: CAPSULE, DELAYED RELEASE
Manufacturer: PD-Rx Pharmaceuticals, Inc.
Category: prescription | Type: HUMAN PRESCRIPTION DRUG LABEL
Date: 20251016

ACTIVE INGREDIENTS: OMEPRAZOLE 20 mg/1 1
INACTIVE INGREDIENTS: FERRIC OXIDE YELLOW; GELATIN; SILICON DIOXIDE; SODIUM LAURYL SULFATE; TITANIUM DIOXIDE; BUTYL ALCOHOL; PROPYLENE GLYCOL; CROSPOVIDONE; HYPROMELLOSES; MAGNESIUM STEARATE; MANNITOL; MEGLUMINE; METHACRYLIC ACID - ETHYL ACRYLATE COPOLYMER (1:1) TYPE A; SHELLAC; POLOXAMER 407; POVIDONE; TRIETHYL CITRATE; D&C RED NO. 28; FD&C BLUE NO. 1; FD&C RED NO. 40; FD&C YELLOW NO. 6

HIGHLIGHTS OF PRESCRIBING INFORMATION

These highlights do not include all the information needed to use OMEPRAZOLE DELAYED-RELEASE CAPSULES safely and effectively. See full prescribing information for OMEPRAZOLE DELAYED-RELEASE CAPSULES.
OMEPRAZOLE delayed-release capsules, for oral use
INITIAL U.S. APPROVAL: 1989

RECENT MAJOR CHANGES

Warnings and Precautions, Interactions with Diagnostic Investigations for Neuroendocrine Tumors (5.10) 03/2014

Indications and Usage, Treatment of Gastroesophageal Reflux Disease (GERD) (adults and pediatric patients) (1.3) 12/2014

Dosage and Administration, Maintenance of Healing of Erosive Esophagitis (2.5) 12/2014

Warnings and Precautions, Acute Interstitial Nephritis (5.3) 12/2014

Warnings and Precautions, Cyanocobalamin (vitamin B-12) Deficiency (5.4) 12/2014

1 INDICATIONS AND USAGE

Omeprazole is a proton pump inhibitor indicated for:

- Treatment in adults of duodenal ulcer (1.1) and gastric ulcer (1.2)
- Treatment in adults and children of gastroesophageal reflux disease (GERD) (1.3) and maintenance of healing of erosive esophagitis (1.4)

The safety and effectiveness of omeprazole in pediatric patients < 1 year of age have not been established. (8.4)

2 DOSAGE AND ADMINISTRATION

Indication | Omeprazole Dose |  | Frequency
Treatment of Active Duodenal Ulcer (2.1) | 20 mg |  | Once daily for 4 weeks. Some patients may require an additional 4 weeks
H. pylori Eradication to Reduce the Risk of Duodenal Ulcer Recurrence (2.2)
Triple Therapy:
Omeprazole | 20 mg |  | Each drug twice daily for 10 days
Amoxicillin | 1000 mg
Clarithromycin | 500 mg
Dual Therapy:
Omeprazole | 40 mg |  | Once daily for 14 days
Clarithromycin | 500 mg |  | Three times daily for 14 days
Gastric Ulcer (2.3) | 40 mg |  | Once daily for 4 to 8 weeks
GERD (2.4) | 20 mg |  | Once daily for 4 to 8 weeks
Maintenance of Healing of Erosive Esophagitis (2.5) | 20 mg |  | Once daily
Pathological Hypersecretory Conditions (2.6) | 60 mg (varies with individual patient) |  | Once daily
Pediatric Patients (2 to 16 years of age) (2.7) | Weight | Dose
GERD | 10 < 20 kg | 10 mg | Once daily
And Maintenance of | ≥ 20 kg | 20 mg
Healing of Erosive Esophagitis

3 DOSAGE FORMS AND STRENGTHS

- Omeprazole delayed-release capsules, 10 mg, 20 mg and 40 mg (3)

4 CONTRAINDICATIONS

Known hypersensitivity to any component of the formulation or substituted benzimidazoles (angioedema and anaphylaxis have occurred) (4)

5 WARNINGS AND PRECAUTIONS

- Symptomatic response does not preclude the presence of gastric malignancy (5.1)
- Atrophic gastritis: has been noted with long-term therapy (5.2)
- Acute interstitial nephritis has been observed in patients taking PPIs. (5.3)
- Cyanocobalamin (vitamin B-12) Deficiency: Daily long-term use (e.g., longer than 3 years) may lead to malabsorption or a deficiency of cyanocobalamin. (5.4)
- PPI therapy may be associated with increased risk of Clostridium difficile associated diarrhea. (5.5)
- Avoid concomitant use of omeprazole with clopidogrel. (5.6)
- Bone Fracture: Long-term and multiple daily dose PPI therapy may be associated with an increased risk for osteoporosis-related fractures of the hip, wrist or spine. (5.7)
- Hypomagnesemia has been reported rarely with prolonged treatment with PPIs. (5.8)
- Avoid concomitant use of omeprazole with St.John’s Wort or rifampin due to the potential reduction in omeprazole concentrations. (5.9,7.3)
- Interactions with diagnostic investigations for Neuroendocrine Tumors: Increases in intragastric pH may result in hypergastrinemia and enterochromaffin-like cell hyperplasia and increased Choromogranin A levels which may interfere with diagnostic investigations for neuroendocrine tumors. (5.10, 12.2)

6 ADVERSE REACTIONS

Adults: Most common adverse reactions (incidence >2%) are

- Headache, abdominal pain, nausea, diarrhea, vomiting, and flatulence. (6)

Pediatric patients (2 to 16 years of age):

Safety profile similar to that in adults, except that respiratory system events and fever were the most frequently reported reactions in pediatric studies. (8.4)

To report SUSPECTED ADVERSE REACTIONS, contact Dr. Reddy’s Laboratories Inc., at 1-888-375-3784 or FDA at 1-800-FDA-1088 or www.fda.gov/medwatch.

7 DRUG INTERACTIONS

- Atazanavir and nelfinavir: omeprazole reduces plasma levels of atazanavir and nelfinavir. Concomitant use is not recommended (7.1)
- Saquinavir: omeprazole increases plasma levels of saquinavir. Monitor for toxicity and consider dose reduction of saquinavir (7.1)
- May interfere with drugs for which gastric pH affects bioavailability (e.g., ketoconazole, iron salts, erlotinib, ampicillin esters, digoxin and mycophenolate mofetil). Patients treated with omeprazole and digoxin may need to be monitored for increases in digoxin toxicity. (7.2)
- Clopidogrel: omeprazole decreases exposure to the active metabolite of clopidogrel. (7.3, 12.3)
- Clopidogrel: Omeprazole decreases exposure to the active metabolite of clopidogrel. (7.3, 12.3)
- Cilostazol: omeprazole increases systemic exposure of cilostazol and one of its active metabolites. Consider dose reduction of cilostazol. (7.3)
- Drugs metabolized by cytochrome P450 (e.g., diazepam, warfarin, phenytoin, cyclosporine, disulfiram, benzodiazepines): omeprazole can prolong their elimination. Monitor and determine need for dose adjustments (7.3)
- Patients treated with proton pump inhibitors and warfarin may need to be monitored for increases in INR and prothrombin time (7.3)
- Combined inhibitor of CYP2C19 and 3A4 (e.g. voriconazole) may raise omeprazole levels (7.3)
- Tacrolimus: omeprazole may increase serum levels of tacrolimus (7.4)
- Methotrexate: Omeprazole may increase serum levels of methotrexate (7.7)

8 USE IN SPECIFIC POPULATIONS

- Pregnancy: Based on animal data may cause fetal harm (8.1)
- Patients with hepatic impairment:

Consider dose reduction, particularly for maintenance of healing erosive esophagitis (12.3)

FULL PRESCRIBING INFORMATION

1 INDICATIONS AND USAGE

1.1 Duodenal Ulcer (adults)

Omeprazole delayed-release capsules are indicated for short-term treatment of active duodenal ulcer in adults. Most patients heal within four weeks. Some patients may require an additional four weeks of therapy.

Omeprazole delayed-release capsules, in combination with clarithromycin and amoxicillin, are indicated for treatment of patients with H. pylori infection and duodenal ulcer disease (active or up to 1-year history) to eradicate H. pylori in adults.

Omeprazole delayed-release capsules, in combination with clarithromycin are indicated for treatment of patients with H. pylori infection and duodenal ulcer disease to eradicate H. pylori in adults.

Eradication of H. pylori has been shown to reduce the risk of duodenal ulcer recurrence [see Clinical Studies (14.1) and Dosage and Administration (2)].

Among patients who fail therapy, Omeprazole delayed-release capsules with clarithromycin are more likely to be associated with the development of clarithromycin resistance as compared with triple therapy. In patients who fail therapy, susceptibility testing should be done. If resistance to clarithromycin is demonstrated or susceptibility testing is not possible, alternative antimicrobial therapy should be instituted. [See Microbiology section (12.4)] , and the clarithromycin package insert, Microbiology section.)

1.2 Gastric Ulcer (adults)

Omeprazole delayed-release capsules are indicated for short-term treatment (4 to 8 weeks) of active benign gastric ulcer in adults for upto 4 weeks. [See Clinical Studies (14.2)]

1.3 Treatment of Gastroesophageal Reflux Disease (GERD) (adults and pediatric patients)

Symptomatic GERD

Omeprazole delayed-release capsules are indicated for the treatment of heartburn and other symptoms associated with GERD in pediatric patients and adults.

Erosive Esophagitis

Omeprazole delayed-release capsules are indicated for the short-term treatment (4 to 8 weeks) of erosive esophagitis that has been diagnosed by endoscopy in pediatric patients and adults. [See Clinical Studies (14.4)]

The efficacy of omeprazole delayed-release capsules used for longer than 8 weeks in these patients has not been established. If a patient does not respond to 8 weeks of treatment, an additional 4 weeks of treatment may be given. If there is recurrence of erosive esophagitis or GERD symptoms (e.g., heartburn), additional 4 to 8 week courses of omeprazole may be considered.

1.4 Maintenance of Healing of Erosive Esophagitis (adults and pediatric patients)

Omeprazole delayed-release capsules are indicated to maintain healing of erosive esophagitis in pediatric patients and adults.

Controlled studies do not extend beyond 12 months. [See Clinical Studies (14.4) ]

1.5 Pathological Hypersecretory Conditions (adults)

Omeprazole delayed-release capsules are indicated for the long-term treatment of pathological hypersecretory conditions (e.g., Zollinger-Ellison syndrome, multiple endocrine adenomas and systemic mastocytosis) in adults.

2 DOSAGE AND ADMINISTRATION

Omeprazole delayed-release capsules should be taken before eating. In the clinical trials, antacids were used concomitantly with omeprazole.

Patients should be informed that the omeprazole delayed-release capsule should be swallowed whole.

For patients unable to swallow an intact capsule, alternative administration options are available [See Dosage and Administration (2.8)].

2.1 Short-Term Treatment of Active Duodenal Ulcer

The recommended adult oral dose of omeprazole delayed-release capsules is 20 mg once daily. Most patients heal within four weeks. Some patients may require an additional four weeks of therapy.

2.2 H. pylori Eradication for the Reduction of the Risk of Duodenal Ulcer Recurrence

Triple Therapy (omeprazole/clarithromycin/amoxicillin) — The recommended adult oral regimen is omeprazole delayed-release capsules 20 mg plus clarithromycin 500 mg plus amoxicillin 1000 mg each given twice daily for 10 days. In patients with an ulcer present at the time of initiation of therapy, an additional 18 days of omeprazole delayed-release capsules 20 mg once daily is recommended for ulcer healing and symptom relief.

Dual Therapy (omeprazole/clarithromycin) — The recommended adult oral regimen is omeprazole delayed-release capsuels 40 mg once daily plus clarithromycin 500 mg three times daily for 14 days. In patients with an ulcer present at the time of initiation of therapy, an additional 14 days of omeprazole delayed-release capsules 20 mg once daily is recommended for ulcer healing and symptom relief.

2.3 Gastric Ulcer

The recommended adult oral dose is 40 mg once daily for 4 to 8 weeks.

2.4 Gastroesophageal Reflux Disease (GERD)

The recommended adult oral dose for the treatment of patients with symptomatic GERD and no esophageal lesions is 20 mg daily for up to 4 weeks. The recommended adult oral dose for the treatment of patients with erosive esophagitis and accompanying symptoms due to GERD is 20 mg daily for 4 to 8 weeks.

2.5 Maintenance of Healing of Erosive Esophagitis

The recommended adult oral dose is 20 mg daily. Controlled studies do not extend beyond 12 months. [See Clinical Studies (14.4)]

2.6 Pathological Hypersecretory Conditions

The dosage of omeprazole delayed-release capsules in patients with pathological hypersecretory conditions varies with the individual patient. The recommended adult oral starting dose is 60 mg once daily. Doses should be adjusted to individual patient needs and should continue for as long as clinically indicated. Doses up to 120 mg three times daily have been administered. Daily dosages of greater than 80 mg should be administered in divided doses. Some patients with Zollinger-Ellison syndrome have been treated continuously with omeprazole delayed-release capsules for more than 5 years.

2.7 Pediatric Patients

For the treatment of GERD and maintenance of healing of erosive esophagitis, the recommended daily dose for pediatric patients 2 to 16 years of age is as follows:

Patient Weight | Omeprazole Daily Dose
10 < 20 kg | 10 mg
≥ 20 kg | 20 mg

On a per kg basis, the doses of omeprazole required to heal erosive esophagitis in pediatric patients are greater than those for adults.

Alternative administrative options can be used for pediatric patients unable to swallow an intact capsule [See Dosage and Administration (2.8)].

2.8 Alternative Administration Options

Omeprazole is available as a delayed-release capsule.

For patients who have difficulty swallowing capsules, the contents of an omeprazole delayed-release capsule can be added to applesauce. One tablespoon of applesauce should be added to an empty bowl and the capsule should be opened. All of the pellets inside the capsule should be carefully emptied on the applesauce. The pellets should be mixed with the applesauce and then swallowed immediately with a glass of cool water to ensure complete swallowing of the pellets. The applesauce used should not be hot and should be soft enough to be swallowed without chewing. The pellets should not be chewed or crushed. The pellets/applesauce mixture should not be stored for future use.

3 DOSAGE FORMS AND STRENGTHS

Omeprazole delayed-release capsules, USP 10 mg are off-white to pale yellow, elliptical to spherical pellets filled in size ‘3’ hard gelatin capsules with opaque lavender coloured cap and opaque yellow coloured body, imprinted on cap ‘OMEPRAZOLE’

10 mg

and on body ‘R157’ with black ink.

Omeprazole delayed-release capsules, USP 20 mg are off-white to pale yellow, elliptical to spherical pellets filled in size ‘2’ hard gelatin capsules with opaque lavender coloured cap and opaque iron grey coloured body, imprinted on cap ‘OMEPRAZOLE’

20 mg

and on body ‘R158’ with black ink.

Omeprazole delayed-release capsules, USP 40 mg are off-white to pale yellow, elliptical to spherical pellets filled in size ‘Oel’ hard gelatin capsules with opaque yellow coloured cap and opaque lavender coloured body, imprinted on cap ‘OMEPRAZOLE’

40 mg

and on body ‘R159’ with black ink.

4 CONTRAINDICATIONS

Omeprazole delayed-release capsules are contraindicated in patients with known hypersensitivity to substituted benzimidazoles or to any component of the formulation. Hypersensitivity reactions may include anaphylaxis, anaphylactic shock, angioedema, bronchospasm, acute interstitial nephritis, and urticaria [see Adverse Reactions (6)].

For information about contraindications of antibacterial agents (clarithromycin and amoxicillin) indicated in combination with omeprazole, refer to the CONTRAINDICATIONS section of their package inserts.

5 WARNINGS AND PRECAUTIONS

5.1 Concomitant Gastric Malignancy

Symptomatic response to therapy with omeprazole does not preclude the presence of gastric malignancy.

5.2 Atrophic Gastritis

Atrophic gastritis has been noted occasionally in gastric corpus biopsies from patients treated long-term with omeprazole.

5.3 Acute Interstitial Nephritis

Acute interstitial nephritis has been observed in patients taking PPIs including omeprazole. Acute interstitial nephritis may occur at any point during PPI therapy and is generally attributed to an idiopathic hypersensitivity reaction. Discontinue omeperazole if acute interstitial nephritis develops [see Contraindications (4) ].

5.4 Cyanocobalamin (vitamin B-12) Deficiency

Daily treatment with any acid-suppressing medications over a long period of time (e.g., longer than 3 years) may lead to malabsorption of cyanocobalamin (vitamin B-12) caused by hypo-or achlorhydria. Rare reports of cyanocobalamin deficiency occurring with acidsuppressing therapy have been reported in the literature. This diagnosis should be considered if clinical symptoms consistent with cyanocobalamin deficiency are observed.

5.5 Clostridium difficile associated diarrhea

Published observational studies suggest that PPI therapy like omeprazole may be associated with an increased risk of Clostridium difficile associated diarrhea, especially in hospitalized patients. This diagnosis should be considered for diarrhea that does not improve [see Adverse Reactions (6.2)].

Patients should use the lowest dose and shortest duration of PPI therapy appropriate to the condition being treated.

Clostridium diffficile associated diarrhea (CDAD) has been reported with use of nearly all antibacterial agents. For more information specific to antibacterial agents (clarithromycin and amoxicillin) indicated for use in combination with omeprazole, refer to WARNINGS and PRECAUTIONS sections of those package inserts.

5.6 Interaction with Clopidogrel

Avoid concomitant use of omeprazole with clopidogrel. Clopidogrel is a prodrug. Inhibition of platelet aggregation by clopidogrel is entirely due to an active metabolite. The metabolism of clopidogrel to its active metabolite can be impaired by use with concomitant medications, such as omeprazole, that inhibit CYP2C19 activity. Concomitant use of clopidogrel with 80 mg omeprazole reduces the pharmacological activity of clopidogrel, even when administered 12 hours apart. When using omeprazole, consider alternative anti-platelet therapy [see Drug Interactions (7.3) and Pharmacokinetics (12.3) ].

5.7 Bone Fracture

Several published observational studies suggest that proton pump inhibitor (PPI) therapy may be associated with an increased risk for osteoporosis-related fractures of the hip, wrist, or spine. The risk of fracture was increased in patients who received high-dose, defined as multiple daily doses, and long-term PPI therapy (a year or longer). Patients should use the lowest dose and shortest duration of PPI therapy appropriate to the condition being treated. Patients at risk for osteoporosis-related fractures should be managed according to established treatment guidelines. [see Dosage and Administration (2) and Adverse Reactions (6.3)]

5.8 Hypomagnesemia

Hypomagnesemia, symptomatic and asymptomatic, has been reported rarely in patients treated with PPIs for at least three months, in most cases after a year of therapy. Serious adverse events include tetany, arrhythmias, and seizures. In most patients, treatment of hypomagnesemia required magnesium replacement and discontinuation of the PPI.

For patients expected to be on prolonged treatment or who take PPIs with medications such as digoxin or drugs that may cause hypomagnesemia (e.g., diuretics), health care professionals may consider monitoring magnesium levels prior to initiation of PPI treatment and periodically. [See Adverse Reactions (6.3)]

5.9 Comcomitant Use of Omeprazole with St John’s Wort or rifampin

Drugs which induce CYP2C19 or CYP3A4 (such as St John’s Wort or rifampin) can substantially decrease omeprazole concentrations. [See Drug Interactions (7.3)]. Avoid concomitant use of omeprazole with St John’s Wort or rifampin.

5.10 Interactions with Diagnostic Investigations for Neuroendocrine Tumors

Serum chromogranin A (CgA) levels increase secondary to drug-induced decreases in gastric acidity. The increased CgA level may cause false positive results in diagnostic investigations for neuroendocrine tumors. Providers should temporarily stop omeprazole treatment before assessing CgA levels and consider repeating the test if initial CgA levels are high. If serial tests are performed (e.g. for monitoring), the same commercial laboratory should be used for testing, as reference ranges between tests may vary.

5.11 Concomitant use of NEXIUM with Methotrexate

Literature suggests that concomitant use of PPIs with methotrexate (primarily at high dose; see methotrexate prescribing information) may elevate and prolong serum levels of methotrexate and/or its metabolite, possibly leading to methotrexate toxicities. In high-dose methotrexate administration a temporary withdrawal of the PPI may be considered in some patients. [see Drug Interactions (7.6)]

6 ADVERSE REACTIONS

6.1 Clinical Trials Experience with Omeprazole Monotherapy

Because clinical trials are conducted under widely varying conditions, adverse reaction rates observed in the clinical trials of a drug cannot be directly compared to rates in the clinical trials of another drug and may not reflect the rates observed in practice.

The safety data described below reflects exposure to omeprazole delayed-release capsules in 3096 patients from worldwide clinical trials (465 patients from US studies and 2,631 patients from international studies). Indications clinically studied in US trials included duodenal ulcer, resistant ulcer, and Zollinger-Ellison syndrome. The international clinical trials were double blind and open-label in design. The most common adverse reactions reported (i.e., with an incidence rate ≥ 2%) from omeprazole-treated patients enrolled in these studies included headache (6.9%), abdominal pain (5.2%), nausea (4%), diarrhea (3.7%), vomiting (3.2%), and flatulence (2.7%).

Additional adverse reactions that were reported with an incidence ≥1% included acid regurgitation (1.9%), upper respiratory infection (1.9%), constipation (1.5%), dizziness (1.5%), rash (1.5%), asthenia (1.3%), back pain (1.1%), and cough (1.1%).

The clinical trial safety profile in patients greater than 65 years of age was similar to that in patients 65 years of age or less.

The clinical trial safety profile in pediatric patients who received omeprazole delayed-release capsules was similar to that in adult patients. Unique to the pediatric population, however, adverse reactions of the respiratory system were most frequently reported in the 2 to 16 year age group (18.5%). Similarly, accidental injuries were reported frequently in the 2 to 16 year age group (3.8%). [See Use in Specific Populations (8.4)]

6.2 Clinical Trials Experience with Omeprazole in Combination Therapy for H. pylori Eradication

In clinical trials using either dual therapy with omeprazole and clarithromycin, or triple therapy with omeprazole, clarithromycin, and amoxicillin, no adverse reactions unique to these drug combinations were observed. Adverse reactions observed were limited to those previously reported with omeprazole, clarithromycin, or amoxicillin alone.

Dual Therapy (omeprazole/clarithromycin)

Adverse reactions observed in controlled clinical trials using combination therapy with omeprazole and clarithromycin (n = 346) that differed from those previously described for omeprazole alone were taste perversion (15%), tongue discoloration (2%), rhinitis (2%), pharyngitis (1%) and flu-syndrome (1%). (For more information on clarithromycin, refer to the clarithromycin prescribing information, Adverse Reactions section).

Triple Therapy (omeprazole/clarithromycin/amoxicillin)

The most frequent adverse reactions observed in clinical trials using combination therapy with omeprazole, clarithromycin, and amoxicillin (n = 274) were diarrhea (14%), taste perversion (10%), and headache (7%). None of these occurred at a higher frequency than that reported by patients taking antimicrobial agents alone. (For more information on clarithromycin or amoxicillin, refer to the respective prescribing information, Adverse Reactions sections).

6.3 Post-marketing Experience

The following adverse reactions have been identified during post-approval use of omeprazole delayed-release capsules. Because these reactions are voluntarily reported from a population of uncertain size, it is not always possible to reliably estimate their actual frequency or establish a causal relationship to drug exposure.

Body As a Whole: Hypersensitivity reactions including anaphylaxis, anaphylactic shock, angioedema, bronchospasm, interstitial nephritis, urticaria, (see also Skin below); fever; pain; fatigue; malaise;

Cardiovascular: Chest pain or angina, tachycardia, bradycardia, palpitations, elevated blood pressure, peripheral edema

Endocrine: Gynecomastia

Gastrointestinal: Pancreatitis (some fatal), anorexia, irritable colon, fecal discoloration, esophageal candidiasis, mucosal atrophy of the tongue, stomatitis, abdominal swelling, dry mouth, microscopic colitis. During treatment with omeprazole, gastric fundic gland polyps have been noted rarely.

These polyps are benign and appear to be reversible when treatment is discontinued. Gastroduodenal carcinoids have been reported in patients with ZE syndrome on long-term treatment with omeprazole. This finding is believed to be a manifestation of the underlying condition, which is known to be associated with such tumors.

Hepatic: Liver disease including hepatic failure (some fatal), liver necrosis (some fatal), hepatic encephalopathy hepatocellular disease, cholestatic disease, mixed hepatitis, jaundice, and elevations of liver function tests [ALT, AST, GGT, alkaline phosphatase, and bilirubin]

Infections and Infestations: Clostridium difficile associated diarrhea

Metabolism and Nutritional disorders: Hypoglycemia, hypomagnesemia, hyponatremia, weight gain

Musculoskeletal: Muscle weakness, myalgia, muscle cramps, joint pain, leg pain, bone fracture

Nervous System/Psychiatric: Psychiatric and sleep disturbances including depression, agitation, aggression, hallucinations, confusion, insomnia, nervousness, apathy, somnolence, anxiety, and dream abnormalities; tremors, paresthesia; vertigo

Respiratory: Epistaxis, pharyngeal pain

Skin: Severe generalized skin reactions including toxic epidermal necrolysis (some fatal), Stevens-Johnson syndrome, and erythema multiforme; photosensitivity; urticaria; rash; skin inflammation; pruritus; petechiae; purpura; alopecia; dry skin; hyperhidrosis

Special Senses: Tinnitus, taste perversion

Ocular: Optic atrophy, anterior ischemic optic neuropathy, optic neuritis, dry eye syndrome, ocular irritation, blurred vision, double vision

Urogenital: Interstitial nephritis, hematuria, proteinuria, elevated serum creatinine, microscopic pyuria, urinary tract infection, glycosuria, urinary frequency, testicular pain

Hematologic: Agranulocytosis (some fatal), hemolytic anemia, pancytopenia, neutropenia, anemia, thrombocytopenia, leukopenia, leucocytosis

7 DRUG INTERACTIONS

7.1 Interference with Antiretroviral Therapy

Concomitant use of atazanavir and nelfinavir with proton pump inhibitors is not recommended. Co-administration of atazanavir with proton pump inhibitors is expected to substantially decrease atazanavir plasma concentrations and may result in a loss of therapeutic effect and the development of drug resistance. Co-administration of saquinavir with proton pump inhibitors is expected to increase saquinavir concentrations, which may increase toxicity and require dose reduction.

Omeprazole has been reported to interact with some antiretroviral drugs. The clinical importance and the mechanisms behind these interactions are not always known. Increased gastric pH during omeprazole treatment may change the absorption of the antiretroviral drug. Other possible interaction mechanisms are via CYP 2C19.

Reduced concentrations of atazanavir and nelfinavir

For some antiretroviral drugs, such as atazanavir and nelfinavir, decreased serum levels have been reported when given together with omeprazole. Following multiple doses of nelfinavir (1250 mg, twice daily) and omeprazole (40 mg daily), AUC was decreased by 36% and 92%, Cmax by 37% and 89% and Cmin by 39% and 75% respectively for nelfinavir and M8. Following multiple doses of atazanavir (400 mg, daily) and omeprazole (40 mg, daily, 2 hr before atazanavir), AUC was decreased by 94%, Cmax by 96%, and Cmin by 95%. Concomitant administration with omeprazole and drugs such as atazanavir and nelfinavir is therefore not recommended.

Increased concentrations of saquinavir

For other antiretroviral drugs, such as saquinavir, elevated serum levels have been reported, with an increase in AUC by 82%, in Cmax by 75%, and in Cmin by 106%, following multiple dosing of saquinavir/ritonavir (1000/100 mg) twice daily for 15 days with omeprazole 40 mg daily co-administered days 11 to 15. Therefore, clinical and laboratory monitoring for saquinavir toxicity is recommended during concurrent use with omeprazole. Dose reduction of saquinavir should be considered from the safety perspective for individual patients.

There are also some antiretroviral drugs of which unchanged serum levels have been reported when given with omeprazole.

7.2 Drugs for which Gastric pH can affect Bioavailability

Due to its effects on gastric acid secretion, omeprazole can reduce the absorption of drugs where gastric pH is an important determinant of theirbioavailability. Like with other drugs that decrease the intragastric acidity, the absorption of drugs such as ketoconazole, atazanavir, iron salts, erlotinib, and mycophenolate mofetil (MMF) can decrease, while the absorption of drugs such as digoxin can increase during treatment with omeprazole. Concomitant treatment with omeprazole (20 mg daily) and digoxin in healthy subjects increased the bioavailability of digoxin by 10% (30% in two subjects). Co-administration of digoxin with omeprazole is expected to increase the systemic exposure of digoxin.

Therefore, patients may need to be monitored when digoxin is taken concomitantly with omeprazole.

Co-administration of omeprazole in healthy subjects and in transplant patients receiving MMF has been reported to reduce the exposure to the active metabolite, mycophenolic acid (MPA), possibly due to a decrease in MMF solubility at an increased gastric pH. The clinical relevance of reduced MPA exposure on organ rejection has not been established in transplant patients receiving omeprazole and MMF. Use omeprazole with caution in transplant patients receiving MMF [see Clinical Pharmacology (12.3)].

7.3 Effects on Hepatic Metabolism/Cytochrome P-450 Pathways

Omeprazole can prolong the elimination of diazepam, warfarin and phenytoin, drugs that are metabolized by oxidation in the liver. There have been reports of increased INR and prothrombin time in patients receiving proton pump inhibitors, including omeprazole, and warfarin concomitantly. Increases in INR and prothrombin time may lead to abnormal bleeding and even death. Patients treated with proton pump inhibitors and warfarin may need to be monitored for increases in INR and prothrombin time.

Although in normal subjects no interaction with theophylline or propranolol was found, there have been clinical reports of interaction with other drugs metabolized via the cytochrome P450 system (e.g., cyclosporine, disulfiram, benzodiazepines). Patients should be monitored to determine if it is necessary to adjust the dosage of these drugs when taken concomitantly with omeprazole.

Concomitant administration of omeprazole and voriconazole (a combined inhibitor of CYP2C19 and CYP3A4) resulted in more than doubling of the omeprazole exposure. Dose adjustment of omeprazole is not normally required. However, in patients with Zollinger-Ellison syndrome, who may require higher doses up to 240 mg/day, dose adjustment may be considered. When voriconazole (400 mg Q12h x 1 day, then 200 mg x 6 days) was given with omeprazole (40 mg once daily x 7 days) to healthy subjects, it significantly increased the steady-state Cmax and AUC0-24 of omeprazole, an average of 2 times (90% CI: 1.8, 2.6) and 4 times (90% CI: 3.3, 4.4) respectively as compared to when omeprazole was given without voriconazole.

Omeprazole acts as an inhibitor of CYP2C19. Omeprazole, given in doses of 40 mg daily for one week to 20 healthy subjects in crossover study, increased Cmax and AUC of cilostazol by 18% and 26% respectively. Cmax and AUC of one of its active metabolites, 3,4-dihydro-cilostazol, which has 4 to 7 times the activity of cilostazol, were increased by 29% and 69% respectively. Co-administration of cilostazol with omeprazole is expected to increase concentrations of cilostazol and its above mentioned active metabolite. Therefore a dose reduction of cilostazol from 100 mg twice daily to 50 mg twice daily should be considered.

Drugs known to induce CYP2C19 or CYP3A4 (such as rifampin) may lead to decreased omeprazole serum levels. In a cross-over study in 12 healthy male subjects, St John’s wort (300 mg three times daily for 14 days), an inducer of CYP3A4, decreased the systemic exposure of omeprazole in CYP2C19 poor metabolisers (Cmax and AUC decreased by 37.5% and 37.9%, respectively) and extensive metabolisers (Cmax and AUC decreased by 49.6% and 43.9%, respectively). Avoid concomitant use of St. John’s Wort or rifampin with omeprazole.

Clopidogrel

Omeprazole is an inhibitor of CYP2C19 enzyme. Clopidogrel is metabolized to its active metabolite in part by CYP2C19. Concomitant use of omeprazole 80 mg results in reduced plasma concentrations of the active metabolite of clopidogrel and a reduction in platelet inhibition. Avoid concomitant administration of omeprazole with clopidogrel. When using omeprazole, consider use of alternative anti-platelet therapy [see Pharmacokinetics (12.3)].

There are no adequate combination studies of a lower dose of omeprazole or a higher dose of clopidogrel in comparison with the approved dose of clopidogrel.

7.4 Tacrolimus

Concomitant administration of omeprazole and tacrolimus may increase the serum levels of tacrolimus.

7.5 Interactions with Investigations of Neuroendocrine Tumors

Drug-induced decrease in gastric acidity results in enterochromaffin-like cell hyperplasia and increased Chromogranin A levels which may interfere with investigations for neuroendocrine tumors. [see Warnings and Precautions (5.10) and Clinical Pharmacology (12)].

7.6 Combination Therapy with Clarithromycin

Concomitant administration of clarithromycin with other drugs can lead to serious adverse reactions due to drug interactions [see Warnings and Precautions in prescribing information for clarithromycin]. Because of these drug interactions, clarithromycin is contraindicated for co-administration with certain drugs [see Contraindications in prescribing information for clarithromycin].

7.7 Methotrexate

Case reports, published population pharmacokinetic studies, and retrospective analyses suggest that concomitant administration of PPIs and methotrexate (primarily at high dose; see methotrexate prescribing information) may elevate and prolong serum levels of methotrexate and/or its metabolite hydroxymethotrexate. However, no formal drug interaction studies of methotrexate with PPIs have been conducted [see Warnings and Precautions (5.11)].

8 USE IN SPECIFIC POPULATIONS

8.1 Pregnancy

Pregnancy Category C

Risk Summary

There are no adequate and well-controlled studies with omeprazole in pregnant women. Available epidemiologic data fail to demonstrate an increased risk of major congenital malformations or other adverse pregnancy outcomes with first trimester omeprazole use.

Teratogenicity was not observed in animal reproduction studies with administration of oral esomeprazole magnesium in rats and rabbits with doses about 68 times and 42 times, respectively, an oral human dose of 40 mg (based on a body surface area basis for a 60 kg person). However, changes in bone morphology were observed in offspring of rats dosed through most of pregnancy and lactation at doses equal to or greater than approximately 34 times an oral human dose of 40 mg (see Animal Data). Because of the observed effect at high doses of esomeprazole magnesium on developing bone in rat studies, omeprazole should be used during pregnancy only if the potential benefit justifies the potential risk to the fetus.

Human Data

Four published epidemiological studies compared the frequency of congenital abnormalities among infants born to women who used omeprazole during pregnancy with the frequency of abnormalities among infants of women exposed to H2-receptor antagonists or other controls.

A population-based retrospective cohort epidemiological study from the Swedish Medical Birth Registry, covering approximately 99% of pregnancies, from 1995-99, reported on 955 infants (824 exposed during the first trimester with 39 of these exposed beyond first trimester, and 131 exposed after the first trimester) whose mothers used omeprazole during pregnancy. The number of infants exposed in utero to omeprazole that had any malformation, low birth weight, low Apgar score, or hospitalization was similar to the number observed in this population. The number of infants born with ventricular septal defects and the number of stillborn infants was slightly higher in the omeprazole-exposed infants than the expected number in this population.

A population-based retrospective cohort study covering all live births in Denmark from 1996-2009, reported on 1,800 live births whose mothers used omeprazole during the first trimester of pregnancy and 837,317 live births whose mothers did not use any proton pump inhibitor. The overall rate of birth defects in infants born to mothers with first trimester exposure to omeprazole was 2.9% and 2.6% in infants born to mothers not exposed to any proton pump inhibitor during the first trimester.

A retrospective cohort study reported on 689 pregnant women exposed to either H2-blockers or omeprazole in the first trimester (134 exposed to omeprazole) and 1,572 pregnant women unexposed to either during the first trimester. The overall malformation rate in offspring born to mothers with first trimester exposure to omeprazole, an H2-blocker, or were unexposed was 3.6%, 5.5% and 4.1% respectively.

A small prospective observational cohort study followed 113 women exposed to omeprazole during pregnancy (89% first trimester exposures). The reported rates of major congenital malformations was 4% for the omeprazole group, 2% for controls exposed to non-teratogens, and 2.8% in disease-paired controls. Rates of spontaneous and elective abortions, preterm deliveries, gestational age at delivery, and mean birth weight were similar among the groups.

Several studies have reported no apparent adverse short-term effects on the infant when single dose oral or intravenous omeprazole was administered to over 200 pregnant women as premedication for cesarean section under general anesthesia.

Animal Data

Reproductive studies conducted with omeprazole in rats at oral doses up to 138 mg/kg/day (about 34 times an oral human dose of 40 mg on a body surface area basis) and in rabbits at doses up to 69 mg/kg/day (about 34 times an oral human dose of 40 mg on a body surface area basis) did not disclose any evidence for a teratogenic potential of omeprazole. In rabbits, omeprazole in a dose range of 6.9 to 69.1 mg/kg/day (about 3.4 to 34 times an oral human dose of 40 mg on a body surface area basis) produced dose-related increases in embryo-lethality, fetal resorptions, and pregnancy disruptions. In rats, dose-related embryo/fetal toxicity and postnatal developmental toxicity were observed in offspring resulting from parents treated with omeprazole at 13.8 to 138 mg/kg/day (about 3.4 to 34 times an oral human doses of 40 mg on a body surface area basis).

Reproduction studies have been performed with esomeprazole magnesium in rats at oral doses up to 280 mg/kg/day (about 68 times an oral human dose of 40 mg on a body surface area basis) and in rabbits at oral doses up to 86 mg/kg/day (about 42 times an oral human dose of 40 mg on a body surface area basis) and have revealed no evidence of impaired fertility or harm to the fetus due to esomeprazole magnesium.

A pre- and postnatal developmental toxicity study in rats with additional endpoints to evaluate bone development was performed with esomeprazole magnesium at oral doses of 14 to 280 mg/kg/day (about 3.4 to 68 times an oral human dose of 40 mg on a body surface area basis). Neonatal/early postnatal (birth to weaning) survival was decreased at doses equal to or greater than 138 mg/kg/day (about 34 times an oral human dose of 40 mg on a body surface area basis). Body weight and body weight gain were reduced and neurobehavioral or general developmental delays in the immediate postweaning timeframe were evident at doses equal to or greater than 69 mg /kg/day (about 17 times an oral human dose of 40 mg on a body surface area basis). In addition, decreased femur length, width and thickness of cortical bone, decreased thickness of the tibial growth plate and minimal to mild bone marrow hypocellularity were noted at doses equal to or greater than 14 mg/kg/day (about 3.4 times an oral human dose of 40 mg on a body surface area basis). Physeal dysplasia in the femur was observed in offspring of rats treated with oral doses of esomeprazole magnesium at doses equal to or greater than 138 mg/kg/day (about 34 times an oral human dose of 40 mg on a body surface area basis).

Effects onmaternal bone were observed in pregnant and lactating rats in the pre- and postnatal toxicity study when esomeprazole magnesiumwas administered at oral doses of 14 to 280 mg /kg/day (about 3.4 to 68 times an oral human dose of 40 mg on a body surface area basis). When rats were dosed from gestational day 7 through weaning on postnatal day 21, a statistically significant decrease in maternal femur weight of up to 14% (as compared to placebo treatment) was observed at doses equal to or greater than 138 mg/kg/day (about 34 times an oral human dose of 40 mg on a body surface area basis).

A pre- and postnatal development study in rats with esomeprazole strontium (using equimolar doses compared to esomeprazole magnesium study) produced similar results in dams and pups as described above.

8.3 Nursing Mothers

Omeprazole is present in human milk. Omeprazole concentrations were measured in breast milk of a woman following oral administration of 20 mg. The peak concentration of omeprazole in breast milk was less than 7% of the peak serum concentration. This concentration would correspond to 0.004 mg of omperazole in 200 mL of milk. Caution should be exercised when omperazole is administered to a nursing woman.

8.4 Pediatric Use

Use of omeprazole in pediatric and adolescent patients 2 to 16 years of age for the treatment of GERD and maintenance of healing of erosive esophagitis is supported by a) extrapolation of results from adequate and well-controlled studies that supported the approval of omeprazole for adults, and b) safety and pharmacokinetic studies performed in pediatric and adolescent patients. [See Clinical Pharmacology, Pharmacokinetics, Pediatric for pharmacokinetic information (12.3) and Dosage and Administration (2) . Adverse Reactions (6.1) and Clinical Studies (14.6)]. The safety and effectiveness of omeprazole for the treatment of GERD in patients < 1 year of age have not been established. The safety and effectiveness of omeprazole for other pediatric uses have not been established.

Juvenile Animal Data In a juvenile rat toxicity study, esomeprazole was administered with both magnesium and strontium salts at oral doses about 34 to 57 times a daily human dose of 40 mg based on body surface area. Increases in death were seen at the high dose, and at all doses of esomeprazole, there were decreases in body weight, body weight gain, femur weight and femur length, and decreases in overall growth [see Nonclinical Toxicology (13.2)].

8.5 Geriatric Use

Omeprazole was administered to over 2000 elderly individuals (≥ 65 years of age) in clinical trials in the U.S. and Europe. There were no differences in safety and effectiveness between the elderly and younger subjects. Other reported clinical experience has not identified differences in response between the elderly and younger subjects, but greater sensitivity of some older individuals cannot be ruled out.

Pharmacokinetic studies have shown the elimination rate was somewhat decreased in the elderly and bioavailability was increased. The plasma clearance of omeprazole was 250 mL/min (about half that of young volunteers) and its plasma half-life averaged one hour, about twice that of young healthy volunteers. However, no dosage adjustment is necessary in the elderly. [See Clinical Pharmacology (12.3)]

8.6 Hepatic Impairment

Consider dose reduction, particularly for maintenance of healing of erosive esophagitis. [See Clinical Pharmacology (12.3)]

8.7 Renal Impairment

No dosage reduction is necessary. [See Clinical Pharmacology (12.3)]

8.8 Asian Population

Consider dose reduction, particularly for maintenance of healing of erosive esophagitis. [See Clinical Pharmacology (12.3)]

10 OVERDOSAGE

Reports have been received of overdosage with omeprazole in humans. Doses ranged up to 2400 mg (120 times the usual recommended clinical dose). Manifestations were variable, but included confusion, drowsiness, blurred vision, tachycardia, nausea, vomiting, diaphoresis, flushing, headache, dry mouth, and other adverse reactions similar to those seen in normal clinical experience. [See Adverse Reactions (6)] Symptoms were transient, and no serious clinical outcome has been reported when omeprazole was taken alone. No specific antidote for omeprazole overdosage is known. Omeprazole is extensively protein bound and is, therefore, not readily dialyzable. In the event of overdosage, treatment should be symptomatic and supportive.

As with the management of any overdose, the possibility of multiple drug ingestion should be considered. For current information on treatment of any drug overdose, contact your local Poison Control Center.

Single oral doses of omeprazole at 1350, 1339, and 1200 mg/kg were lethal to mice, rats, and dogs, respectively. Animals given these doses showed sedation, ptosis, tremors, convulsions, and decreased activity, body temperature, and respiratory rate and increased depth of respiration.

11 DESCRIPTION

The active ingredient in omeprazole delayed-release capsules is a substituted benzimidazole, 5-methoxy-2-[[(4-methoxy-3, 5-dimethyl-2-pyridinyl) methyl] sulfinyl]-1H-benzimidazole, a compound that inhibits gastric acid secretion. Its empirical formula is C17H19N3O3S, with a molecular weight of 345.42. The structural formula is:

Omeprazole is a white to off-white powder. Melts between 150°C and 160°C with decomposition. It is soluble in dichloromethane, sparingly soluble in methanol and in alcohol.

Omeprazole delayed-release capsules meets USP Dissolution Test 2.

Omeprazole is supplied as delayed-release capsules for oral administration. Each delayed-release capsule contains either 10 mg, 20 mg or 40 mg of omeprazole in the form of enteric-coated granules with the following inactive ingredients: crospovidone, hypromellose, magnesium stearate, mannitol, meglumine, methacrylic acid copolymer, poloxamer, povidone and triethyl citrate.

The capsule shells contains: D&C Red No. 28, FD&C Blue No. 1, FD&C Red No. 40, FD&C Yellow No. 6, yellow iron oxide, gelatin, silicon dioxide, sodium lauryl sulphate and titanium dioxide. Imprinting ink contains: D&C Yellow No. 10 aluminum lake, FD&C Blue No. 1 aluminum lake, FD&C Blue No. 2 aluminum lake, FD&C Red No. 40 aluminum lake, n-butyl alcohol, pharmaceutical glaze, propylene glycol, SDA-3A alcohol and synthetic black iron oxide.

12 CLINICAL PHARMACOLOGY

12.1 Mechanism of Action

Omeprazole belongs to a class of antisecretory compounds, the substituted benzimidazoles, that suppress gastric acid secretion by specific inhibition of the H+/K+ ATPase enzyme system at the secretory surface of the gastric parietal cell. Because this enzyme system is regarded as the acid (proton) pump within the gastric mucosa, omeprazole has been characterized as a gastric acid-pump inhibitor, in that it blocks the final step of acid production. This effect is dose-related and leads to inhibition of both basal and stimulated acid secretion irrespective of the stimulus. Animal studies indicate that after rapid disappearance from plasma, omeprazole can be found within the gastric mucosa for a day or more.

12.2 Pharmacodynamics

Antisecretory Activity

After oral administration, the onset of the antisecretory effect of omeprazole occurs within one hour, with the maximum effect occurring within two hours. Inhibition of secretion is about 50% of maximum at 24 hours and the duration of inhibition lasts up to 72 hours. The antisecretory effect thus lasts far longer than would be expected from the very short (less than one hour) plasma half-life, apparently due to prolonged binding to the parietal H+/K+ ATPase enzyme. When the drug is discontinued, secretory activity returns gradually, over 3 to 5 days. The inhibitory effect of omeprazole on acid secretion increases with repeated once-daily dosing, reaching a plateau after four days.

Results from numerous studies of the antisecretory effect of multiple doses of 20 mg and 40 mg of omeprazole in normal volunteers and patients are shown below. The “max” value represents determinations at a time of maximum effect (2 to 6 hours after dosing), while “min” values are those 24 hours after the last dose of omeprazole.

Table 1

Range of Mean Values from Multiple Studies of the Mean Antisecretory Effects of Omeprazole After Multiple Daily Dosing

 | Omeprazole 20 mg |  | Omeprazole 40 mg
Parameter | Max | Min | Max | Min
% Decrease in Basal Acid Output | 78* | 58 to 80 | 94* | 80 to 93
% Decrease in Peak Acid Output | 79* | 50 to 59 | 88* | 62 to 68
% Decrease in 24–hr Intragastric Acidity |  | 80 to 97 |  | 92 to 94

* Single Studies

Single daily oral doses of omeprazole ranging from a dose of 10 mg to 40 mg have produced 100% inhibition of 24-hour intragastric acidity in some patients.

Serum Gastrin Effects

In studies involving more than 200 patients, serum gastrin levels increased during the first 1 to 2 weeks of once-daily administration of therapeutic doses of omeprazole in parallel with inhibition of acid secretion. No further increase in serum gastrin occurred with continued treatment. In comparison with histamine H2-receptor antagonists, the median increases produced by 20 mg doses of omeprazole were higher (1.3 to 3.6 fold vs. 1.1 to 1.8 fold increase). Gastrin values returned to pretreatment levels, usually within 1 to 2 weeks after discontinuation of therapy.

Increased gastrin causes enterochromaffin-like cell hyperplasia and increased serum Chromogranin A (CgA) levels. The increased CgA levels may cause false positive results in diagnostic investigations for neuroendocrine tumors.

Enterochromaffin-like (ECL) Cell Effects

Human gastric biopsy specimens have been obtained from more than 3000 patients treated with omeprazole in long-term clinical trials. The incidence of ECL cell hyperplasia in these studies increased with time; however, no case of ECL cell carcinoids, dysplasia, or neoplasia has been found in these patients. [See Clinical Pharmacology (12)] However, these studies are of insufficient duration and size to rule out the possible influence of long-term administration of omeprazole on the development of any premalignant or malignant conditions.

Other Effects

Systemic effects of omeprazole in the CNS, cardiovascular and respiratory systems have not been found to date. Omeprazole, given in oral doses of 30 or 40 mg for 2 to 4 weeks, had no effect on thyroid function, carbohydrate metabolism, or circulating levels of parathyroid hormone, cortisol, estradiol, testosterone, prolactin, cholecystokinin or secretin.

No effect on gastric emptying of the solid and liquid components of a test meal was demonstrated after a single dose of omeprazole 90 mg. In healthy subjects, a single I.V. dose of omeprazole (0.35 mg/kg) had no effect on intrinsic factor secretion. No systematic dose-dependent effect has been observed on basal or stimulated pepsin output in humans.

However, when intragastric pH is maintained at 4 or above, basal pepsin output is low, and pepsin activity is decreased.

As do other agents that elevate intragastric pH, omeprazole administered for 14 days in healthy subjects produced a significant increase in the intragastric concentrations of viable bacteria. The pattern of the bacterial species was unchanged from that commonly found in saliva. All changes resolved within three days of stopping treatment.

The course of Barrett’s esophagus in 106 patients was evaluated in a U.S. double-blind controlled study of omeprazole 40 mg twice daily for 12 months followed by 20 mg twice daily for 12 months or ranitidine 300 mg twice daily for 24 months. No clinically significant impact on Barrett’s mucosa by antisecretory therapy was observed. Although neosquamous epithelium developed during antisecretory therapy, complete elimination of Barrett’s mucosa was not achieved. No significant difference was observed between treatment groups in development of dysplasia in Barrett’s mucosa and no patient developed esophageal carcinoma during treatment. No significant differences between treatment groups were observed in development of ECL cell hyperplasia, corpus atrophic gastritis, corpus intestinal metaplasia, or colon polyps exceeding 3 mm in diameter [See Clinical Pharmacology (12)].

12.3 Pharmacokinetics

Absorption

Omeprazole delayed-release capsules contain an enteric-coated granule formulation of omeprazole (because omeprazole is acid-labile), so that absorption of omeprazole begins only after the granules leave the stomach. Absorption is rapid, with peak plasma levels of omeprazole occurring within 0.5 to 3.5 hours. Peak plasma concentrations of omeprazole and AUC are approximately proportional to doses up to 40 mg, but because of a saturable first-pass effect, a greater than linear response in peak plasma concentration and AUC occurs with doses greater than 40 mg. Absolute bioavailability (compared with intravenous administration) is about 30 to 40% at doses of 20 to 40 mg, due in large part to presystemic metabolism. In healthy subjects the plasma half-life is 0.5 to 1 hour, and the total body clearance is 500 to 600 mL/min.

The bioavailability of omeprazole increases slightly upon repeated administration of omeprazole delayed-release capsules.

Omeprazole delayed-release capsule 40 mg was bioequivalent when administered with and without applesauce. However, Omeprazole delayed-release capsule 20 mg was not bioequivalent when administered with and without applesauce. When administered with applesauce, a mean 25% reduction in Cmax was observed without a significant change in AUC for Omeprazole delayed-release capsule 20 mg. The clinical relevance of this finding is unknown.

Distribution

Protein binding is approximately 95%.

Metabolism

Omeprazole is extensively metabolized by the cytochrome P450 (CYP) enzyme system.

Excretion

Following single dose oral administration of a buffered solution of omeprazole, little if any unchanged drug was excreted in urine. The majority of the dose (about 77%) was eliminated in urine as at least six metabolites. Two were identified as hydroxyomeprazole and the corresponding carboxylic acid. The remainder of the dose was recoverable in feces. This implies a significant biliary excretion of the metabolites of omeprazole. Three metabolites have been identified in plasma — the sulfide and sulfone derivatives of omeprazole, and hydroxyomeprazole. These metabolites have very little or no antisecretory activity.

Combination Therapy with Antimicrobials

Omeprazole 40 mg daily was given in combination with clarithromycin 500 mg every 8 hours to healthy adult male subjects. The steady state plasma concentrations of omeprazole were increased (Cmax, AUC0-24, and T1/2 increases of 30%, 89% and 34% respectively) by the concomitant administration of clarithromycin. The observed increases in omeprazole plasma concentration were associated with the following pharmacological effects. The mean 24-hour gastric pH value was 5.2 when omeprazole was administered alone and 5.7 when co-administered with clarithromycin.

The plasma levels of clarithromycin and 14-hydroxy-clarithromycin were increased by the concomitant administration of omeprazole. For clarithromycin, the mean Cmax was 10% greater, the mean Cmin was 27% greater, and the mean AUC0-8 was 15% greater when clarithromycin was administered with omeprazole than when clarithromycin was administered alone. Similar results were seen for 14-hydroxy-clarithromycin, the mean Cmax was 45% greater, the mean Cmin was 57% greater, and the mean AUC0-8 was 45% greater. Clarithromycin concentrations in the gastric tissue and mucus were also increased by concomitant administration of omeprazole.

Table 2

Clarithromycin Tissue Concentrations 2 hours after Dose^1

Tissue | Clarithromycin | Clarithromycin + Omeprazole
Antrum | 10.48 ± 2.01 (n = 5) | 19.96 ± 4.71 (n=5)
Fundus | 20.81 ± 7.64 (n = 5) | 24.25 ± 6.37 (n= 5)
Mucus | 4.15 ± 7.74 (n = 4) | 39.29 ± 32.79 (n=4)

^1mean ± SD (mcg/g)

Concomitant Use with Clopidogrel

In a crossover clinical study, 72 healthy subjects were administered clopidogrel (300 mg loading dose followed by 75 mg per day) alone and with omeprazole (80 mg at the same time as clopidogrel) for 5 days. The exposure to the active metabolite of clopidogrel was decreased by 46% (Day 1) and 42% (Day 5) when clopidogrel and omeprazole were administered together.

Results from another crossover study in healthy subjects showed a similar pharmacokinetic interaction between clopidogrel (300 mg loading dose/75 mg daily maintenance dose) and omeprazole 80 mg daily when co-administered for 30 days. Exposure to the active metabolite of clopidogrel was reduced by 41% to 46% over this time period.

In another study, 72 healthy subjects were given the same doses of clopidogrel and 80 mg omeprazole but the drugs were administered 12 hours apart; the results were similar, indicating that administering clopidogrel and omeprazole at different times does not prevent their interaction.

Concomitant Use with Mycophenolate Mofetil

Administration of omeprazole 20 mg twice daily for 4 days and a single 1000 mg dose of MMF approximately one hour after the last dose of omeprazole to 12 healthy subjects in a cross-over study resulted in a 52% reduction in the Cmax and 23% reduction in the AUC of MPA.

Special Populations

Geriatric Population

The elimination rate of omeprazole was somewhat decreased in the elderly, and bioavailability was increased. Omeprazole was 76% bioavailable when a single 40 mg oral dose of omeprazole (buffered solution) was administered to healthy elderly volunteers, versus 58% in young volunteers given the same dose. Nearly 70% of the dose was recovered in urine as metabolites of omeprazole and no unchanged drug was detected. The plasma clearance of omeprazole was 250 mL/min (about half that of young volunteers) and its plasma half-life averaged one hour, about twice that of young healthy volunteers.

Pediatric Use

The pharmacokinetics of omeprazole have been investigated in pediatric patients 2 to 16 years of age:

Table 3

Pharmacokinetic Parameters of Omeprazole Following Single and Repeated Oral Administration in Pediatric Populations Compared with Adults

Single or Repeated Oral Dosing /Parameter | Children† ≤ 20 kg 2 to 5 years | Children†> 20 kg 6 to 16 years | Adults‡(mean 76 kg) 23 to 29 years(n=12)
 | 10 mg | 20 mg
Single Dosing
Cmax* (ng/mL) | 288 (n=10) | 495 (n=49) | 668
AUC* (ng h/mL) | 511 (n=7) | 1140 (n=32) | 1220
Repeated Dosing
Cmax* (ng/mL) | 539 (n=4) | 851 (n=32) | 1458
AUC * (ng h/mL) | 1179 (n=2) | 2276 (n=23) | 3352

Note: * = plasma concentration adjusted to an oral dose of 1 mg/kg.

† Data from single and repeated dose studies

‡ Data from a single and repeated dose study

Doses of 10, 20 and 40 mg omeprazole as enteric-coated granules

Following comparable mg/kg doses of omeprazole, younger children (2 to 5 years of age) have lower AUCs than children 6 to16 years of age or adults; AUCs of the latter two groups did not differ. [See Dosage and Administration (2)]

Hepatic Impairment

In patients with chronic hepatic disease, the bioavailability increased to approximately 100% compared with an I.V. dose, reflecting decreased first-pass effect, and the plasma half-life of the drug increased to nearly 3 hours compared with the half-life in normals of 0.5 to 1 hour. Plasma clearance averaged 70 mL/min, compared with a value of 500 to 600 mL/min in normal subjects. Dose reduction, particularly where maintenance of healing of erosive esophagitis is indicated, for the hepatically impaired should be considered.

Renal Impairment

In patients with chronic renal impairment, whose creatinine clearance ranged between 10 and 62 mL/min/1.73 m^2, the disposition of omeprazole was very similar to that in healthy volunteers, although there was a slight increase in bioavailability. Because urinary excretion is a primary route of excretion of omeprazole metabolites, their elimination slowed in proportion to the decreased creatinine clearance. No dose reduction is necessary in patients with renal impairment.

Asian Population

In pharmacokinetic studies of single 20 mg omeprazole doses, an increase in AUC of approximately four-fold was noted in Asian subjects compared with Caucasians. Dose reduction, particularly where maintenance of healing of erosive esophagitis is indicated, for Asian subjects should be considered.

12.4 Microbiology

Omeprazole and clarithromycin dual therapy and omeprazole, clarithromycin and amoxicillin triple therapy have been shown to be active against most strains of Helicobacter pyloriin vitro and in clinical infections as described in the Indications and Usage section 1.1.

Helicobacter

Helicobacter pylori- Pretreatment Resistance

Clarithromycin pretreatment resistance rates were 3.5% (4/113) in the omeprazole/clarithromycin dual therapy studies (4 and 5) and 9.3% (41/439) in omeprazole/clarithromycin/amoxicillin triple therapy studies (1, 2, and 3).

Amoxicillin pretreatment susceptible isolates (≤ 0.25 mcg/mL) were found in 99.3% (436/439) of the patients in the omeprazole/clarithromycin/amoxicillin triple therapy studies (1, 2, and 3). Amoxicillin pretreatment minimum inhibitory concentrations (MICs) > 0.25 mcg/mL occurred in 0.7% (3/439) of the patients, all of whom were in the clarithromycin and amoxicillin study arm. One patient had an unconfirmed pretreatment amoxicillin minimum inhibitory concentration (MIC) of > 256 mcg/mL by Etest®.

Table 4

Clarithromycin Susceptibility Test Results and Clinical/Bacteriological Outcomes

Clarithromycin Susceptibility Test Results and Clinical/Bacteriological Outcomesa
Clarithromycin Pretreatment Results |  |  | Clarithromycin Post-treatment Results
 | H. pylori negative – eradicated | H. pylori positive – not eradicated Post-treatment susceptibility results
 | H. pylori negative – eradicated | S b | I b | R b | No MIC
Dual Therapy – (omeprazole 40 mg once daily/clarithromycin 500 three times daily for 14 days followed by omeprazole 20 mg once daily for another 14 days) (Studies 4,5)
Susceptible b108 | 72 | 1 |  | 26 | 9
Intermediate b1 |  |  |  | 1
Resistant b4 |  |  |  | 4
Triple Therapy – (omeprazole 20 mg twice daily/clarithromycin 500 mg twice daily/amoxicillin 1 g twice daily for 10 days – Studies 1, 2,3; followed by omeprazole 20 mg once daily for another 18 days – Studies 1,2)
Susceptible b171 | 153 | 7 |  | 3 | 8
Intermediate b
Resistant b14 | 4 | 1 |  | 6 | 3

aIncludes only patients with pretreatment clarithromycin susceptibility test results

b Susceptible (S) MIC ≤ 0.25 mcg/mL, Intermediate (I) MIC 0.5 to 1 mcg/mL, Resistant (R) MIC ≥ 2 mcg/mL

Patients not eradicated of H. pylori following omeprazole/clarithromycin/amoxicillin triple therapy or omeprazole/clarithromycin dual therapy will likely have clarithromycin resistant H. pylori isolates. Therefore, clarithromycin susceptibility testing should be done, if possible. Patients with clarithromycin resistant H. pylori should not be treated with any of the following: omeprazole/clarithromycin dual therapy, omeprazole/clarithromycin/amoxicillin triple therapy, or other regimens which include clarithromycin as the sole antimicrobial agent.

Amoxicillin Susceptibility Test Results and Clinical/Bacteriological Outcomes

In the triple therapy clinical trials, 84.9% (157/185) of the patients in the omeprazole/clarithromycin/amoxicillin treatment group who had pretreatment amoxicillin susceptible MICs (≤ 0.25 mcg/mL) were eradicated of H. pylori and 15.1% (28/185) failed therapy. Of the 28 patients who failed triple therapy, 11 had no post-treatment susceptibility test results and 17 had post-treatment H. pylori isolates with amoxicillin susceptible MICs. Eleven of the patients who failed triple therapy also had post-treatment H. pylori isolates with clarithromycin resistant MICs.

Susceptibility Test for Helicobacter pylori

For susceptibility testing information about Helicobacter pylori, see Microbiology section in prescribing information for clarithromycin and amoxicillin.

Effects on Gastrointestinal Microbial Ecology

Decreased gastric acidity due to any means including proton pump inhibitors, increases gastric counts of bacteria normally present in the gastrointestinal tract. Treatment with proton pump inhibitors may lead to slightly increased risk of gastrointestinal infections such as Salmonella and Campylobacter and, in hospitalized patients, possibly Clostridium difficile.

13 NONCLINICAL TOXICOLOGY

13.1 Carcinogenesis, Mutagenesis, Impairment Of Fertility

In two 24-month carcinogenicity studies in rats, omeprazole at daily doses of 1.7, 3.4, 13.8, 44 and 140.8 mg/kg/day (about 0.4 to 34 times a human dose of 40 mg/day, as expressed on a body surface area basis) produced gastric ECL cell carcinoids in a dose-related manner in both male and female rats; the incidence of this effect was markedly higher in female rats, which had higher blood levels of omeprazole. Gastric carcinoids seldom occur in the untreated rat. In addition, ECL cell hyperplasia was present in all treated groups of both sexes. In one of these studies, female rats were treated with 13.8 mg omeprazole/kg/day (about 3.4 times a human dose of 40 mg/day, based on body surface area) for one year, and then followed for an additional year without the drug. No carcinoids were seen in these rats. An increased incidence of treatment-related ECL cell hyperplasia was observed at the end of one year (94% treated vs 10% controls). By the second year the difference between treated and control rats was much smaller (46% vs 26%) but still showed more hyperplasia in the treated group. Gastric adenocarcinoma was seen in one rat (2%). No similar tumor was seen in male or female rats treated for two years. For this strain of rat no similar tumor has been noted historically, but a finding involving only one tumor is difficult to interpret. In a 52-week toxicity study in Sprague-Dawley rats, brain astrocytomas were found in a small number of males that received omeprazole at dose levels of 0.4, 2, and 16 mg/kg/day (about 0.1 to 3.9 times the human dose of 40 mg/day, based on a body surface area basis). No astrocytomas were observed in female rats in this study. In a 2-year carcinogenicity study in Sprague-Dawley rats, no astrocytomas were found in males or females at the high dose of 140.8 mg/kg/day (about 34 times the human dose of 40 mg/day on a body surface area basis). A 78-week mouse carcinogenicity study of omeprazole did not show increased tumor occurrence, but the study was not conclusive. A 26-week p53 (+/-) transgenic mouse carcinogenicity study was not positive.

Omeprazole was positive for clastogenic effects in an in vitro human lymphocyte chromosomal aberration assay, in one of two in vivo mouse micronucleus tests, and in an in vivo bone marrow cell chromosomal aberration assay. Omeprazole was negative in the in vitro Ames test, an in vitro mouse lymphoma cell forward mutation assay, and an in vivo rat liver DNA damage assay.

Omeprazole at oral doses up to 138 mg/kg/day in rats (about 34 times an oral human dose of 40 mg on a body surface area basis) was found to have no effect on fertility and reproductive performance.

In 24-month carcinogenicity studies in rats, a dose-related significant increase in gastric carcinoid tumors and ECL cell hyperplasia was observed in both male and female animals [See Warnings and Precautions (5)] Carcinoid tumors have also been observed in rats subjected to fundectomy or long-term treatment with other proton pump inhibitors or high doses of H2-receptor antagonists.

13.2 Animal Toxicology and/or Pharmacology

Reproduction Studies

Reproductive Toxicology Studies

Reproductive studies conducted with omeprazole in rats at oral doses up to 138 mg/kg/day (about 34 times the human dose of 40 mg/day on a body surface area basis) and in rabbits at doses up to 69 mg/kg/day (about 34 times the human dose on a body surface area basis) did not disclose any evidence for a teratogenic potential of omeprazole. In rabbits, omeprazole in a dose range of 6.9 to 69.1 mg/kg/day (about 3.4 to 34 times the human dose of 40 mg/day on a body surface area basis) produced dose-related increases in embryo-lethality, fetal resorptions, and pregnancy disruptions. In rats, dose-related embryo/fetal toxicity and postnatal developmental toxicity were observed in offspring resulting from parents treated with omeprazole at 13.8 to 138 mg/kg/day (about 3.4 to 34 times the human dose of 40 mg/day on a body surface area basis) [see Pregnancy, Animal Data (8.1)].

Juvenile Animal Study

A 28-day toxicity study with a 14-day recovery phase was conducted in juvenile rats with esomeprazole magnesium at doses of 70 to 280 mg /kg/day (about 17 to 68 times a daily oral human dose of 40 mg on a body surface area basis). An increase in the number of deaths at the high dose of 280 mg /kg/day was observed when juvenile rats were administered esomeprazole magnesium from postnatal day 7 through postnatal day 35. In addition, doses equal to or greater than 140 mg/kg/day (about 34 times a daily oral human dose of 40 mg on a body surface area basis), produced treatment-related decreases in body weight (approximately 14%) and body weight gain, decreases in femur weight and femur length, and affected overall growth. Comparable findings described above have also been observed in this study with another esomeprazole salt, esomeprazole strontium, at equimolar doses of esomeprazole.

14 CLINICAL STUDIES

14.1 Duodenal Ulcer Disease

Active Duodenal Ulcer— In a multicenter, double-blind, placebo-controlled study of 147 patients with endoscopically documented duodenal ulcer, the percentage of patients healed (per protocol) at 2 and 4 weeks was significantly higher with omeprazole 20 mg once daily than with placebo (p ≤ 0.01).

Treatment of Active Duodenal Ulcer % of Patients Healed

 | Omeprazole 20 mg a.m. | Placebo a.m.
 | (n=99) | (n=48)
Week 2 | *41 | 13
Week 4 | *75 | 27

*(p ≤ 0.01)

Complete daytime and nighttime pain relief occurred significantly faster (p ≤ 0.01) in patients treated with omeprazole 20 mg than in patients treated with placebo. At the end of the study, significantly more patients who had received omeprazole had complete relief of daytime pain (p ≤ 0.05) and nighttime pain (p ≤ 0.01).

In a multicenter, double-blind study of 293 patients with endoscopically documented duodenal ulcer, the percentage of patients healed (per protocol) at 4 weeks was significantly higher with omeprazole 20 mg once daily than with ranitidine 150 mg b.i.d. (p < 0.01).

Treatment of Active Duodenal Ulcer % of Patients Healed

 | Omeprazole | Ranitidine
 | 20 mg a.m. | 150 mg twice daily
 | (n = 145) | (n = 148)
Week 2 | 42 | 34
Week 4 | *82 | 63

*(p < 0.01)

Healing occurred significantly faster in patients treated with omeprazole than in those treated with ranitidine 150 mg b.i.d. (p < 0.01).

In a foreign multinational randomized, double-blind study of 105 patients with endoscopically documented duodenal ulcer, 20 mg and 40 mg of omeprazole were compared with 150 mg b.i.d. of ranitidine at 2, 4 and 8 weeks. At 2 and 4 weeks both doses of omeprazole were statistically superior (per protocol) to ranitidine, but 40 mg was not superior to 20 mg of omeprazole, and at 8 weeks there was no significant difference between any of the active drugs.

Treatment of Active Duodenal Ulcer % of Patients Healed

 | Omeprazole |  | Ranitidine
 | 20 mg (n=34) | 40 mg (n=36) | 150 mg twice daily (n=35)
Week 2 | *83 | *83 | 53
Week 4 | *97 | *100 | 82
Week 8 | 100 | 100 | 94

*(p ≤ 0.01)

H. pylori Eradication in Patients with Duodenal Ulcer Disease

Triple Therapy(omeprazole/clarithromycin/amoxicillin)— Three U.S., randomized, double-blind clinical studies in patients with H. pylori infection and duodenal ulcer disease (n=558) compared omeprazole plus clarithromycin plus amoxicillin with clarithromycin plus amoxicillin. Two studies (1 and 2) were conducted in patients with an active duodenal ulcer, and the other study (3) was conducted in patients with a history of a duodenal ulcer in the past 5 years but without an ulcer present at the time of enrollment. The dose regimen in the studies was omeprazole 20 mg twice daily plus clarithromycin 500 mg twice daily plus amoxicillin 1 g twice daily for 10 days; or clarithromycin 500 mg twice daily, plus amoxicillin 1 g twice daily for 10 days. In studies 1 and 2, patients who took the omeprazole regimen also received an additional 18 days of omeprazole 20 mg once daily. Endpoints studied were eradication of H. pylori and duodenal ulcer healing (studies 1 and 2 only). H. pylori status was determined by CLOtest®, histology and culture in all three studies. For a given patient, H. pylori was considered eradicated if at least two of these tests were negative, and none was positive.

The combination of omeprazole plus clarithromycin plus amoxicillin was effective in eradicating H. pylori.

Table 5

Per-Protocol and Intent-to-Treat H. pylori Eradication Rates % of Patients Cured [95% Confidence Interval]

Omeprazole +clarithromycin+amoxicillin |  |  | Clarithromycin +amoxicillin
 | Per-Protocol† | Intent-to-Treat‡ | Per-Protocol† | Intent-to-Treat‡
Study 1 | *77 [64, 86] | *69 [57, 79] | 43 [31, 56] | 37 [27, 48]
Study 1 | (n = 64) | (n = 80) | (n = 67) | (n = 84)
Study 2 | *78 [67, 88] | *73 [61, 82] | 41 [29, 54] | 36 [26, 47]
Study 2 | (n = 65) | (n = 77) | (n = 68) | (n = 83)
Study 3 | *90 [80, 96] | *83 [74, 91] | 33 [24, 44] | 32 [23, 42]
Study 3 | (n = 69) | (n = 84) | (n = 93) | (n = 99)

† Patients were included in the analysis if they had confirmed duodenal ulcer disease (active ulcer, studies 1 and 2; history of ulcer within 5 years, study 3) and H. pylori infection at baseline defined as at least two of three positive endoscopic tests from CLOtest®, histology, and/or culture. Patients were included in the analysis if they completed the study. Additionally, if patients dropped out of the study due to an adverse event related to the study drug, they were included in the analysis as failures of therapy. The impact of eradication on ulcer recurrence has not been assessed in patients with a past history of ulcer.

‡ Patients were included in the analysis if they had documented H. pylori infection at baseline and had confirmed duodenal ulcer disease. All dropouts were included as failures of therapy.

*(p < 0.05) versus clarithromycin plus amoxicillin.

Dual Therapy (omeprazole /clarithromycin)

Four randomized, double-blind, multi-center studies (4, 5, 6, and 7) evaluated omeprazole 40 mg once daily plus clarithromycin 500 mg three times daily for 14 days, followed by omeprazole 20 mg once daily, (studies 4, 5, and 7) or by omeprazole 40 mg once daily (Study 6) for an additional 14 days in patients with active duodenal ulcer associated with H. pylori. Studies 4 and 5 were conducted in the U.S. and Canada and enrolled 242 and 256 patients, respectively. H. pylori infection and duodenal ulcer were confirmed in 219 patients in Study 4 and 228 patients in Study 5. These studies compared the combination regimen to omeprazole and clarithromycin monotherapies. Studies 6 and 7 were conducted in Europe and enrolled 154 and 215 patients, respectively. H. pylori infection and duodenal ulcer were confirmed in 148 patients in Study 6 and 208 patients in Study 7. These studies compared the combination regimen with omeprazole monotherapy. The results for the efficacy analyses for these studies are described below. H. pylori eradication was defined as no positive test (culture or histology) at 4 weeks following the end of treatment, and two negative tests were required to be considered eradicated of H. pylori. In the per-protocol analysis, the following patients were excluded: dropouts, patients with missing H. pylori tests post-treatment, and patients that were not assessed for H. pylori eradication because they were found to have an ulcer at the end of treatment.

The combination of omeprazole and clarithromycin was effective in eradicating H. pylori.

Table 6

H. pylori Eradication Rates (Per-Protocol Analysis at 4 to 6 Weeks)

% of Patients Cured [95% Confidence Interval]

 | Omeprazole+Clarithromycin | Omeprazole | Clarithromycin
U.S. Studies
Study 4 | 74 [60, 85]†‡ | 0 [0, 7] | 31 [18, 47]
Study 4 | (n = 53) | (n=54) | (n = 42)
Study 5 | 64 [51, 76]†‡ | 0 [0, 6] | 39 [24, 55]
Study 5 | (n = 61) | (n = 59) | (n = 44)
Non U.S. Studies
Study 6 | 83 [71, 92]‡ | 1 [0, 7] | N/A
Study 6 | (n = 60) | (n = 74) | N/A
Study 7 | 74 [64, 83]‡ | 1 [0,6] | N/A

† Statistically significantly higher than clarithromycin monotherapy (p < 0.05)

‡ Statistically significantly higher than omeprazole monotherapy (p < 0.05)

Ulcer healing was not significantly different when clarithromycin was added to omeprazole therapy compared with omeprazole therapy alone.

The combination of omeprazole and clarithromycin was effective in eradicating H. pylori and reduced duodenal ulcer recurrence.

Table 7

Duodenal Ulcer Recurrence Rates by H. pylori Eradication Status % of Patients with Ulcer Recurrence

 | H. pylori eradicated# | H. pylori not eradicated#
U.S. Studies†
6 months post-treatment
Study 4 | *35 | 60
Study 4 | (n = 49) | (n = 88)
Study 5 | *8 | 60
Study 5 | (n = 53) | (n = 106)
Non U.S. Studies‡
6 months post-treatment
Study 6 | *5 | 46
Study 6 | (n=43) | (n=78)
Study 7 | *6 | 43
Study 7 | (n=53) | (n=107)
12 months post-treatment
Study 6 | *5 | 68
Study 6 | (n=39) | (n=71)

# H. pylori eradication status assessed at same time point as ulcer recurrence

† Combined results for omeprazole + clarithromycin, omeprazole, and clarithromycin treatment arms

‡ Combined results for omeprazole + clarithromycin and omeprazole treatment arms

* (p ≤ 0.01) versus proportion with duodenal ulcer recurrence who were not H. pylori eradicated

14.2 Gastric Ulcer

In a U.S. multicenter, double-blind, study of omeprazole 40 mg once daily, 20 mg once daily, and placebo in 520 patients with endoscopically diagnosed gastric ulcer, the following results were obtained.

Treatment of Gastric Ulcer
 | % of Patients Healed
 | (All Patients Treated)
 | Omeprazole | Omeprazole
 | 20 mg once daily | 40 mg once daily | Placebo
 | (n=202) | (n=214) | (n=104)
Week 4 | 47.5 ** | 55.6 ** | 30.8
Week 8 | 74.8 ** | 82.7 **,+ | 48.1

**(p < 0.01) omeprazole 40 mg or 20 mg versus placebo

+(p < 0.05) omeprazole 40 mg versus 20 mg

For the stratified groups of patients with ulcer size less than or equal to 1 cm, no difference in healing rates between 40 mg and 20 mg was detected at either 4 or 8 weeks. For patients with ulcer size greater than 1 cm, 40 mg was significantly more effective than 20 mg at 8 weeks.

In a foreign, multinational, double-blind study of 602 patients with endoscopically diagnosed gastric ulcer, omeprazole 40 mg once daily, 20 mg once daily, and ranitidine 150 mg twice a day were evaluated.

Treatment of Gastric Ulcer
 | % of Patients Healed
 | (All Patients Treated)
 | Omeprazole | Omeprazole | Ranitidine
 | 20 mg once daily | 40 mg once daily | 150 twice daily
 | (n=200) | (n=187) | (n=199)
Week 4 | 63.5 | 78.1**,++ | 56.3
Week 8 | 81.5 | 91.4 **,++ | 78.4

** (p < 0.01) omeprazole 40 mg versus ranitidine

++ (p < 0.01) omerpazole 40 mg versus 20 mg

14.3 Gastroesophageal Reflux Disease (GERD)

Symptomatic GERD

A placebo-controlled study was conducted in Scandinavia to compare the efficacy of omeprazole 20 mg or 10 mg once daily for up to 4 weeks in the treatment of heartburn and other symptoms in GERD patients without erosive esophagitis. Results are shown below.

 | % Successful Symptomatic Outcomea
 | Omeprazole | Omeprazole | Placebo
 | 20 mg a.m. | 10 mg a.m. | a.m.
All patients | 46*,† | 31† | 13
 | (n=205) | (n=199) | (n=105)
Patients with confirmed GERD | 56*,† | 36† | 14
 | (n=115) | (n=109) | (n=59)

a Defined as complete resolution of heartburn

*(p < 0.005) versus 10 mg

†(p < 0.005) versus placebo

14.4 Erosive Esophagitis

In a U.S. multicenter double-blind placebo controlled study of 20 mg or 40 mg of omeprazole delayed-release capsules in patients with symptoms of GERD and endoscopically diagnosed erosive esophagitis of grade 2 or above, the percentage healing rates (per protocol) were as follows:

Week | 20 mg Omeprazole | 40 mg Omeprazole | Placebo
 | (n=83) | (n=87) | (n=43)
4 | 39** | 45** | 7
8 | 74** | 75** | 14

**(p < 0.01) omeprazole versus placebo

In this study, the 40 mg dose was not superior to the 20 mg dose of omeprazole in the percentage healing rate. Other controlled clinical trials have also shown that omeprazole is effective in severe GERD. In comparisons with histamine H2-receptor antagonists in patients with erosive esophagitis, grade 2 or above, omeprazole in a dose of 20 mg was significantly more effective than the active controls. Complete daytime and nighttime heartburn relief occurred significantly faster (p < 0.01) in patients treated with omeprazole than in those taking placebo or histamine H2- receptor antagonists.

In this and five other controlled GERD studies, significantly more patients taking 20 mg omeprazole (84%) reported complete relief of GERD symptoms than patients receiving placebo (12%).

Long Term Maintenance of Healing of Erosive Esophagitis

In a U.S. double-blind, randomized, multicenter, placebo controlled study, two dose regimens of omeprazole were studied in patients with endoscopically confirmed healed esophagitis. Results to determine maintenance of healing of erosive esophagitis are shown below.

Life Table Analysis
 | Omeprazole | Omeprazole
 | 20 mg once daily | 20 mg 3 days per week | Placebo
 | (n=138) | (n = 137) | (n = 131)
Percent in endoscopic remission at 6 months | *70 | 34 | 11

*(p < 0.01) omeprazole 20 mg once daily versus omeprazole 20 mg 3 consecutive days per week or placebo.

In an international multicenter double-blind study, omeprazole 20 mg daily and 10 mg daily were compared with ranitidine 150 mg twice daily in patients with endoscopically confirmed healed esophagitis. The table below provides the results of this study for maintenance of healing of erosive esophagitis.

Life Table Analysis
 | Omeprazole | Omeprazole | Ranitidine
 | 20 mg once daily | 10 mg once daily | 150 mg twice daily
 | (n=131) | (n = 133) | (n = 128)
Percent in endoscopic remission at 12 months | *77 | ‡58 | 46

* (p = 0.01) omeprazole 20 mg once daily. versus omeprazole 10 mg once daily or ranitidine.

‡ (p = 0.03) omepazole 10 mg once daily. versus ranitidine.

In patients who initially had grades 3 or 4 erosive esophagitis, for maintenance after healing 20 mg daily of omeprazole was effective, while 10 mg did not demonstrate effectiveness.

14.5 Pathological Hypersecretory Conditions

In open studies of 136 patients with pathological hypersecretory conditions, such as Zollinger-Ellison (ZE) syndrome with or without multiple endocrine adenomas, omeprazole delayed-release capsules significantly inhibited gastric acid secretion and controlled associated symptoms of diarrhea, anorexia, and pain. Doses ranging from 20 mg every other day to 360 mg per day maintained basal acid secretion below 10 mEq/hr in patients without prior gastric surgery, and below 5 mEq/hr in patients with prior gastric surgery.

Initial doses were titrated to the individual patient need, and adjustments were necessary with time in some patients [See Dosage and Administration (2)]. Omeprazole was well tolerated at these high dose levels for prolonged periods (> 5 years in some patients). In most ZE patients, serum gastrin levels were not modified by omeprazole. However, in some patients serum gastrin increased to levels greater than those present prior to initiation of omeprazole therapy. At least 11 patients with ZE syndrome on long-term treatment with omeprazole developed gastric carcinoids. These findings are believed to be a manifestation of the underlying condition, which is known to be associated with such tumors, rather than the result of the administration of omeprazole. [See Adverse Reactions (6)]

14.6 Pediatric GERD

Symptomatic GERD

The effectiveness of omeprazole for the treatment of nonerosive GERD in pediatric patients 2 to 16 years of age is based in part on data obtained from 125 pediatric patients in an uncontrolled Phase III study. [See Use in Specific Populations (8.4)]

The study enrolled 113 pediatric patients 2 to 16 years of age with a history of symptoms suggestive of nonerosive GERD. Patients were administered a single dose of omeprazole (10 mg or 20 mg, based on body weight) for 4 weeks either as an intact capsule or as an open capsule in applesauce. Successful response was defined as no moderate or severe episodes of either pain-related symptoms or vomiting/regurgitation during the last 4 days of treatment. Results showed success rates of 60% (9/15; 10 mg omeprazole) and 59% (58/98; 20 mg omeprazole), respectively.

Healing of Erosive Esophagitis

In an uncontrolled, open-label dose-titration study, healing of erosive esophagitis in pediatric patients 1 to 16 years of age required doses that ranged from 0.7 to 3.5 mg/kg/day (80 mg/day). Doses were initiated at 0.7 mg/kg/day. Doses were increased in increments of 0.7 mg/kg/day (if intraesophageal pH showed a pH of < 4 for less than 6% of a 24-hour study). After titration, patients remained on treatment for 3 months. Forty-four percent of the patients were healed on a dose of 0.7 mg/kg body weight; most of the remaining patients were healed with 1.4 mg/kg after an additional 3 months’ treatment. Erosive esophagitis was healed in 51 of 57 (90%) children who completed the first course of treatment in the healing phase of the study. In addition, after 3 months of treatment, 33% of the children had no overall symptoms, 57% had mild reflux symptoms, and 40% had less frequent regurgitation/vomiting.

Maintenance of Healing of Erosive Esophagitis

In an uncontrolled, open-label study of maintenance of healing of erosive esophagitis in 46 pediatric patients, 54% of patients required half the healing dose. The remaining patients increased the healing dose (0.7 to a maximum of 2.8 mg/kg/day) either for the entire maintenance period, or returned to half the dose before completion. Of the 46 patients who entered the maintenance phase, 19 (41%) had no relapse. In addition, maintenance therapy in erosive esophagitis patients resulted in 63% of patients having no overall symptoms.

15 REFERENCES

1. National Committee for Clinical Laboratory Standards. Methods for Dilution Antimicrobial Susceptibility Tests for Bacteria That Grow Aerobically—Fifth Edition. Approved Standard NCCLS Document M7-A5, Vol, 20, No. 2, NCCLS, Wayne, PA, January 2000.

16 HOW SUPPLIED/STORAGE AND HANDLING

Omeprazole delayed-release capsules, USP 20 mg are off-white to pale yellow, elliptical to spherical pellets filled in size ‘2’ hard gelatin capsules with opaque lavender coloured cap and opaque iron grey coloured body, imprinted on cap ‘OMEPRAZOLE’

20 mg

and on body ‘R158’ with black ink.

The capsules are supplied in bottles of:

NDC 43063-743-14 Bottles of 14

NDC 43063-743-30 Bottles of 30

NDC 43063-743-60 Bottles of 60

NDC 43063-743-90 Bottles of 90

Storage

Store omeprazole delayed-release capsules in a tight container protected from light and moisture.

Store at 20° to 25°C (68° to 77°F) [See USP Controlled Room Temperature].

17 PATIENT COUNSELING INFORMATION

See FDA-Approved Medication Guide

Omeprazole delayed-release capsules should be taken before eating. Patients should be informed that the omeprazole delayed-release capsules should be swallowed whole.

For patients who have difficulty swallowing capsules, the contents of an omeprazole delayed-release capsule can be added to applesauce. One tablespoon of applesauce should be added to an empty bowl and the capsule should be opened. All of the pellets inside the capsule should be carefully emptied on the applesauce. The pellets should be mixed with the applesauce and then swallowed immediately with a glass of cool water to ensure complete swallowing of the pellets. The applesauce used should not be hot and should be soft enough to be swallowed without chewing. The pellets should not be chewed or crushed. The pellets/applesauce mixture should not be stored for future use.

Advise patients to immediately report and seek care for diarrhea that does not improve. This may be a sign of Clostridium difficile associated diarrhea [see Warnings and Precautions (5.5)].

Advise patients to immediately report and seek care for any cardiovascular or neurological symptoms including palpitations, dizziness, seizures, and tetany as these may be signs of hypomagnesemia [see Warnings and Precautions (5.8)]

MEDICATION GUIDE

OMEPRAZOLE DELAYED-RELEASE CAPSULES, USP

Read this Medication Guide before you start taking omeprazole delayed-release capsules and each time you get a refill. There may be new information. This information does not take the place of talking with your doctor about your medical condition or your treatment.

What is the most important information I should know about omeprazole delayed-release capsules?

Omeprazole delayed-release capsules may help your acid-related symptoms, but you could still have serious stomach problems. Talk with your doctor.

Omeprazole delayed-release capsules can cause serious side effects, including:

- Diarrhea. Omeprazole delayed-release capsules may increase your risk of getting severe diarrhea. This diarrhea may be caused by an infection (Clostridium difficile) in your intestines.

Call your doctor right away if you have watery stool, stomach pain, and fever that does not go away.

- Bone fractures. People who take multiple daily doses of proton pump inhibitor medicines for a long period of time (a year or longer) may have an increased risk of fractures of the hip, wrist, or spine. You should take omeprazole delayed-release capsules exactly as prescribed, at the lowest dose possible for your treatment and for the shortest time needed. Talk to your doctor about your risk of bone fracture if you take omeprazole delayed-release capsules.

Omeprazole delayed-release capsules can have other serious side effects. See “What are the possible side effects of omeprazole delayed-release capsules?”

What is omeprazole delayed-release capsule?

Omeprazole delayed-release capsule is a prescription medicine called a proton pump inhibitor (PPI). Omeprazole delayed-release capsules reduces the amount of acid in your stomach.

Omeprazole delayed-release capsules are used in adults:

- for up to 8 weeks for the healing of duodenal ulcers. The duodenal area is the area where food passes when it leaves the stomach.
- with certain antibiotics for 10 to 14 days to treat an infection caused by bacteria called H. pylori. If needed, your doctor may decide to prescribe another 14 to 18 days of omeprazole delayed-release capsules by itself after the antibiotics. Sometimes H. pylori bacteria can cause duodenal ulcers. The infection needs to be treated to prevent the ulcers from coming back.
- for up to 8 weeks for healing stomach ulcers
- for up to 4 weeks to treat heartburn and other symptoms that happen with gastroesophageal reflux disease (GERD).
- GERD happens when acid in your stomach backs up into the tube (esophagus) that connects your mouth to your stomach. This may cause a burning feeling in your chest or throat, sour taste, or burping.
- for up to 8 weeks to heal acid-related damage to the lining of the esophagus (called erosive esophagitis or EE). If needed, your doctor may decide to prescribe another 4 weeks of omeprazole delayed-release capsules.
- to maintain healing of the esophagus. It is not known if omeprazole delayed-release capsules are safe and effective when used for longer than 12 months (1 year) for this purpose.
- for the long-term treatment of conditions where your stomach makes too much acid. This includes a rare condition called Zollinger-Ellison Syndrome.

For children 1 to 16 years of age, omeprazole delayed-release capsules are used:

- for up to 4 weeks to treat heartburn and other symptoms that happen with gastroesophageal reflux disease (GERD).
- for up to 8 weeks to treat gastroesophageal reflux disease (GERD) with acid-related damage to the lining of the esophagus [called erosive esophagitis (or EE) due to acid-mediated GERD].
- to maintain healing of the esophagus. It is not known if omeprazole delayed-release capsules are safe and effective when used longer than 12 months (1 year) for this purpose.

For children 1 month to less than 12 months (1 year) of age, omeprazole delayed-release capsules are used:

- for up to 6 weeks to treat gastroesophageal reflux disease (GERD) with acid-related damage to the lining of the esophagus [called erosive esophagitis (or EE) due to acid-mediated GERD]. It is not known if omeprazole delayed-release capsules are safe and effective for other uses in children 1 month to less than 12 months (1 year) of age, or in children less than 1 month of age.

Who should not take omeprazole delayed-release capsules? Do not take omeprazole delayed-release capsules if you:

- are allergic to omeprazole or any of the ingredients in omeprazole delayed-release capsules. See the end of this Medication Guide for a complete list of ingredients in omeprazole delayed-release capsules.
- are allergic to any other Proton Pump Inhibitor (PPI) medicine.
- are taking a medicine that contains rilpivirine (EDURANT, COMPLERA) used to treat HIV-1 (Human Immunodeficiency Virus).

What should I tell my doctor before taking omeprazole delayed-release capsules?

Before taking omeprazole delayed-release capsules, tell your doctor about all of your medical conditions including if you:

- have been told that you have low magnesium levels in your blood
- have liver problems
- have any other medical conditions
- are pregnant or plan to become pregnant. It is not known if omeprazole delayed-release capsules will harm your unborn baby.
- are breastfeeding or plan to breastfeed. Omeprazole delayed-release capsules can pass into your breast milk and may harm your baby. You and your doctor should decide if you will take omeprazole delayed-release capsules or breastfeed. You should not do both. Talk to your doctor about the best way to feed your baby if you breastfeed.
- Tell your doctor about all of the medicines you take including prescription and over-the-counter medicines, vitamins and herbal supplements. Omeprazole delayed-release capsules may affect how other medicines work, and other medicines may affect how omeprazole delayed-release capsules works. Especially tell your doctor if you take an antibiotic that contains clarithromycin or amoxicillin, or if you take clopidogrel (Plavix), methotrexate (Otrxup, Rasuvo, Trexall), St. John’s Wort (Hypericum perforatum), or rifampin (Rimactane, Rifater, Rifamate).

Know the medicines that you take. Keep a list of them to show your doctor and pharmacist when you get a new medicine.

How should I take omeprazole delayed-release capsules?

- Take omeprazole delayed-release capsules exactly as prescribed by your doctor.
- Do not change your dose or stop omeprazole delayed-release capsules without talking to your doctor.
- Omeprazole delayed-release capsules are usually taken 1 time each day. Your doctor will tell the time of the day to take omeprazole delayed-release capsules, based on your medical condition.
- Take omeprazole delayed-release capsules before a meal.
- Antacids may be taken with omeprazole delayed-release capsules.

Omeprazole Delayed-Release Capsules

- Swallow omeprazole delayed-release capsules whole. Do not chew or crush omeprazole delayed-release capsules.
- If you have trouble swallowing a whole capsule, you can open the capsule and take the contents in applesauce. See the "Instructions for Use" at the end of this Medication Guide for instructions on how to take omeprazole delayed-release capsules with applesauce.

If you miss a dose of omeprazole delayed-release capsules, take it as soon as you remember. If it is almost time for your next dose, do not take the missed dose. Take the next dose at your regular time. Do not take 2 doses at the same time to make up for the missed dose.

If you take too much omeprazole delayed-release capsules, call your doctor or your poison control center right away or go to the nearest emergency room.

What are the possible side effects of omeprazole delayed-release capsules?

Omeprazole delayed-release capsules can cause serious side effects, including:

See “What is the most important information I should know about omeprazole delayed-release capsules?”

- Vitamin B-12 deficiency. Omeprazole delayed-release capsules reduces the amount of acid in your stomach. Stomach acid is needed to absorb vitamin B-12 properly. Talk with your doctor about the possibility of vitamin B-12 deficiency if you have been on omeprazole delayed-release capsules for a long time (more than 3 years).
- Low magnesium levels in your body. This problem can be serious. Low magnesium can happen in some people who take a proton pump inhibitor (PPI) medicine for at least 3 months. If low magnesium levels happen, it is usually after a year of treatment. You may or may not have symptoms of low magnesium.

You may or may not have symprtoms of low magnesium. Tell your doctor right away if you develop any of these symptoms:

- seizures
- dizziness
- abnormal or fast heart beat
- jitteriness
- jerking movements or shaking (tremors)
- muscle weakness
- spasms of the hands and feet
- cramps or muscle aches
- spasm of the voice box

Your doctor may check the level of magnesium in your body before you start taking omeprazole delayed-release capsules or during treatment if you will be taking omeprazole delayed-release capsules for a long period of time.

The most common side effects with omeprazole delayed-release capsules in adults and children include:

- headache
- stomach pain
- nausea
- diarrhea
- vomiting
- gas

In addition to the side effects listed above, the most common side effects in children 2 to 16 years of age include:

- respiratory system events
- fever

Other side effects:

Serious allergic reactions. Tell your doctor if you get any of the following symptoms with omeprazole delayed-release capsules:

- rash
- face swelling
- throat tightness
- difficulty breathing

Your doctor may stop omeprazole delayed-release capsules if these symptoms happen. Tell your doctor if you have any side effect that bothers you or that does not go away. These are not all the possible side effects with omeprazole delayed-release capsules. For more information, ask your doctor or pharmacist. Call your doctor for medical advice about side effects. You may report side effects to FDA at 1-800-FDA-1088.

How should I store omeprazole delayed-release capsules?

- Store omeprazole delayed-release capsules at room temperature between 20° to 25°C (68° to 77°F).
- Keep the container of omeprazole delayed-release capsules closed tightly.
- Keep the container of omeprazole delayed-release capsules dry and away from light.

Keep omeprazole delayed-release capsules and all medicines out of the reach of children.

General information about the safe and effective use of omeprazole delayed-release capsules

Medicines are sometimes prescribed for purposes other than those listed in a Medication Guide. Do not use omeprazole delayed-release capsules for a condition for which it was not prescribed. Do not give omeprazole delayed-release capsules to other people, even if they have the same symptoms you have. It may harm them.

This Medication Guide summarizes the most important information about omeprazole delayed-release capsules. For more information, ask your doctor. You can ask your doctor or pharmacist for information that is written for healthcare professionals.

What are the ingredients in omeprazole delayed-release capsules?

Active ingredient in omeprazole delayed-release capsules delayed-release capsules: omeprazole

Inactive ingredients in omeprazole delayed-release capsules: Crospovidone, hypromellose, magnesium stearate, mannitol, meglumine, methacrylic acid copolymer, poloxamer, povidone and triethyl citrate.

The capsule shells contains: D&C Red No. 28, FD&C Blue No. 1, FD&C Red No. 40,FD&C Yellow No. 6, yellow iron oxide, gelatin, silicon dioxide, sodium lauryl sulphate and titanium dioxide. Imprinting ink contains: D&C Yellow No. 10 aluminum lake, FD&C Blue No. 1 aluminum lake, FD&C Blue No. 2 aluminum lake, FD&C Red No. 40 aluminum lake, n-butyl alcohol, pharmaceutical glaze, propylene glycol, SDA-3A alcohol and synthetic black iron oxide.

For more information, call 1-888-375-3784.

This Medication has been approved by the U.S. Food and Drug Administration.

To reorder additional Medication Guides, contact Dr. Reddy’s Customer Service at 1-866-733-3952.

Rx Only

Manufactured by:

Dr. Reddy’s Laboratories Limited

Bachupally – 500 090 INDIA

Revised: 0316

PACKAGE LABEL

Omeprazole Delayed-Release Capsules, USP 20 mg